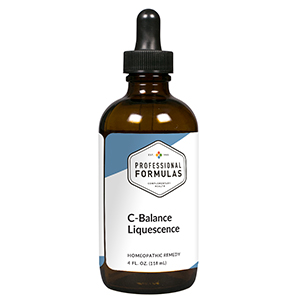 DRUG LABEL: C-Balance Liquescence
NDC: 63083-3022 | Form: LIQUID
Manufacturer: Professional Complementary Health Formulas
Category: homeopathic | Type: HUMAN OTC DRUG LABEL
Date: 20190815

ACTIVE INGREDIENTS: CITRUS AURANTIUM FRUIT RIND 2 [hp_X]/118 mL; AMANITA MUSCARIA FRUITING BODY 3 [hp_X]/118 mL; ASCORBIC ACID 3 [hp_X]/118 mL; LEMON JUICE 3 [hp_X]/118 mL; ECHINACEA ANGUSTIFOLIA WHOLE 3 [hp_X]/118 mL; ECHINACEA PURPUREA WHOLE 3 [hp_X]/118 mL; MALPIGHIA GLABRA WHOLE 3 [hp_X]/118 mL; PETROSELINUM CRISPUM ROOT 3 [hp_X]/118 mL; ROSA CANINA FRUIT 3 [hp_X]/118 mL; SOLANUM TUBEROSUM WHOLE 3 [hp_X]/118 mL; CAPSICUM 4 [hp_X]/118 mL; BOS TAURUS BONE MARROW 6 [hp_X]/118 mL; GOLDENSEAL 6 [hp_X]/118 mL
INACTIVE INGREDIENTS: ALCOHOL; WATER

T22

ACTIVE INGREDIENTS

Citrus vulgaris 2X
Agaricus muscarius 3X
Ascorbicum acidum 3X
Citrus limonum 3X
Echinacea angustifolia 3X
Echinacea purpurea 3X
Malpighia glabra 3X
Petroselinum sativum 3X
Rosa canina 3X
Solanum tuberosum 3X
Capsicum annuum 4X
Bone marrow 6X
Hydrastis canadensis 6X

QUESTIONS

Professional Formulas

PO Box 2034 Lake Oswego, OR 97035

INDICATIONS

For the temporary relief of fatigue, tingling, numbness, itchy skin, shortness of breath, cough, nausea, diarrhea, or occasional headache.*

PURPOSE

*Claims based on traditional homeopathic practice, not accepted medical evidence. Not FDA evaluated.

WARNINGS

Consult a doctor if condition worsens or if symptoms persist. Keep out of the reach of children. In case of overdose, get medical help or contact a poison control center right away. If pregnant or breastfeeding, ask a healthcare professional before use.

Keep out of the reach of children.

PREGNANCY OR BREAST FEEDING

If pregnant or breastfeeding, ask a healthcare professional before use.

DIRECTIONS

Place drops under tongue 30 minutes before/after meals. Adults and children 12 years and over: Take one full dropper up to 2 times per day. Consult a physician for use in children under 12 years of age.

OTHER INFORMATION

Tamper resistant. If seal is broken, do not use. After opening, close container tightly and store at room temperature away from heat.

INACTIVE INGREDIENTS

20% ethanol, purified water.

LABEL

Est 1985

Professional Formulas

Complementary Health

C-Balance Liquescence

Homeopathic Remedy

4 FL. OZ. (118 mL)